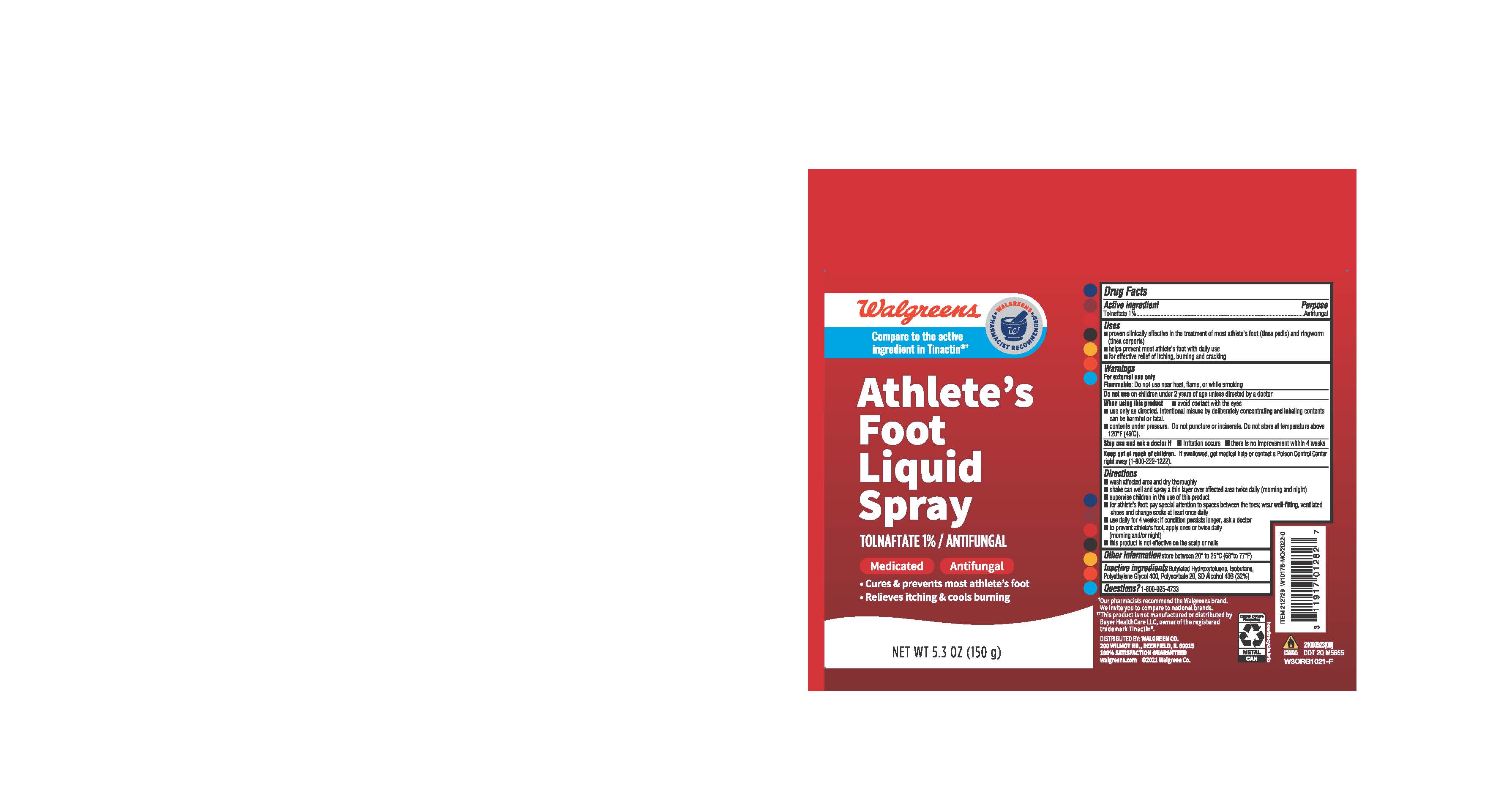 DRUG LABEL: Walgreens Athletes Foot
NDC: 0363-0155 | Form: AEROSOL, SPRAY
Manufacturer: Walgreens
Category: otc | Type: HUMAN OTC DRUG LABEL
Date: 20241211

ACTIVE INGREDIENTS: TOLNAFTATE 1 g/100 g
INACTIVE INGREDIENTS: POLYSORBATE 20; BUTYLATED HYDROXYTOLUENE; ISOBUTANE; DEHYDRATED ALCOHOL; POLYETHYLENE GLYCOL 400

Walgreens Athletes Foot Liquid Spray

ACTIVE INGREDIENT

Tolnaftate 1%

PURPOSE

Antifungal

INDICATIONS AND USAGE

proven clinically effective in the treatment of most athlete’s foot (tinea pedis) and ringworm (tinea corporis)

helps prevent most athlete's foot with daily use

for effective relief of itching, burning and cracking

WARNINGS

For External Use Only

Flammable: Do not use near heat, flame, or while smoking

Do not use on children under 2 years of age unless directed by a doctor

When using this product

Avoid contact with eyes

Use only as directed. Intentional misuse by deliberately concentrating and inhaling contents can be harmful or fatal.

Contents under pressure.

Do not puncture or incinerate. Do not store at temperature above 120°C F (49°C).

Stop use and ask doctor if

Irritation occurs

There is no improvement within 4 weeks

KEEP OUT OF REACH OF CHILDREN

If swallowed, get medical help or contact a Poison Control Center right away (1-800-222-1222)

DOSAGE AND ADMINISTRATION

Wash affected area and dry thoroughly

Shake can well and spray a thin layer over affected area twice daily (morning and night)

Supervise children in the use of this product

For athlete's foot: pay special attention to spaces between the toes: wear well- fitting, ventilated shoes and change socks at least once daily

Use daily for 4 weeks: if condition persists longer, ask a doctor

To prevent athlete's foot: apply once or twice daily (Morning and/or night)

This product is not effective on the scalp or nails

OTHER SAFETY INFORMATION

Store between 20°C to 25 °C (68° to 77°F)

INACTIVE INGREDIENT

Butylated Hydroxytoluene, Isobutane, polyethylene Glycol 400, Polysorbate 20, SD Alcohol 40B (32%)

QUESTIONS

1-800-925-4733